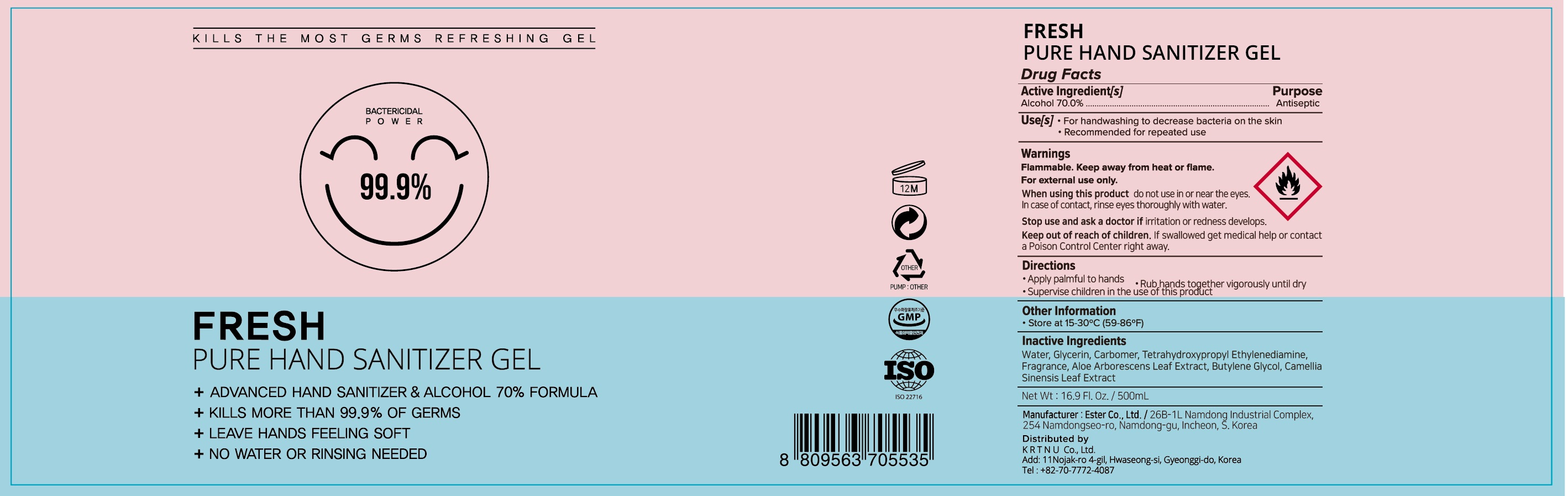 DRUG LABEL: FRESH PURE HAND SANITIZER
NDC: 74004-040 | Form: GEL
Manufacturer: Ester Co., Ltd.
Category: otc | Type: HUMAN OTC DRUG LABEL
Date: 20201111

ACTIVE INGREDIENTS: ALCOHOL 350 g/500 mL
INACTIVE INGREDIENTS: WATER; GLYCERIN; CARBOMER HOMOPOLYMER, UNSPECIFIED TYPE; EDETOL; ALOE ARBORESCENS LEAF; BUTYLENE GLYCOL; GREEN TEA LEAF

ACTIVE INGREDIENT

Active ingredients: ALCOHOL 70%

INACTIVE INGREDIENT

Inactive ingredients:

Water, Glycerin, Carbomer, Tetrahydroxypropyl Ethylenediamine, Fragrance, Aloe Arborescens Leaf Extract, Butylene Glycol, Camellia Sinensis Leaf Extract

PURPOSE

Purpose: ANTISEPTIC

WARNINGS

Flammable, Keep away from fire or flame

For external use only

When using this product do not use in or near the eyes.
In case of contact, rinse eyes thoroughly with water.

Stop use and ask a doctor if irritation or redness develops.

Keep out of reach of children. If swallowed get medical help or contact a Poison Control Center right away.

KEEP OUT OF REACH OF CHILDREN

Keep our of reach of children. If swallowed get medical help or contact a Poison Control Center right away.

Uses

For handwashing when water is not available to decrease bacteria on the skin
- After changing diapers
- After assisting ill persons
- Before contact with a person under medical care or treatment
- Recommended for repeated use

Directions

- Apply palmful to hands
- Rub hands together vigorously until dry
- Supervise children in the use of this product

Other Information

Store at room temperature: 15°~30 °C (59°~86 °F)